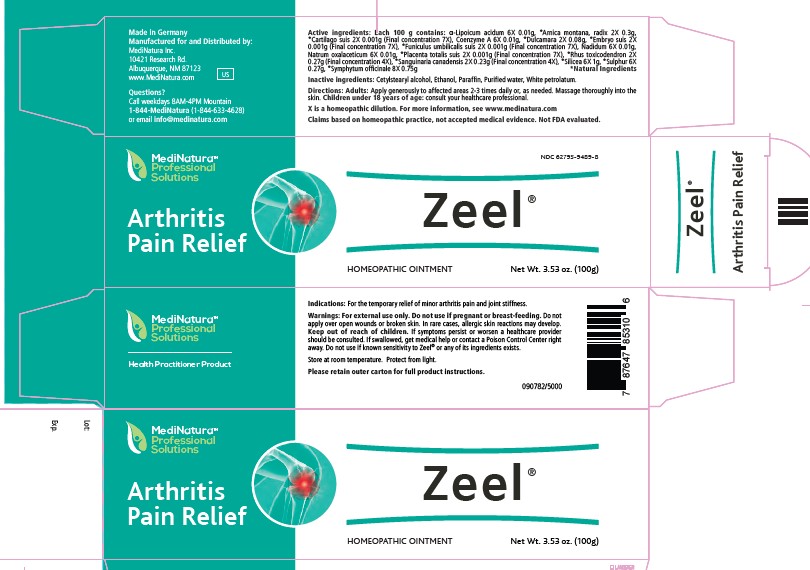 DRUG LABEL: Zeel
NDC: 62795-9489 | Form: OINTMENT
Manufacturer: MediNatura Inc
Category: homeopathic | Type: HUMAN OTC DRUG LABEL
Date: 20230928

ACTIVE INGREDIENTS: ALPHA LIPOIC ACID 6 [hp_X]/1 g; ARNICA MONTANA WHOLE 2 [hp_X]/1 g; SUS SCROFA CARTILAGE 2 [hp_X]/1 g; COENZYME A 6 [hp_X]/1 g; SOLANUM DULCAMARA TOP 2 [hp_X]/1 g; SUS SCROFA EMBRYO 2 [hp_X]/1 g; SUS SCROFA UMBILICAL CORD 2 [hp_X]/1 g; NADIDE 6 [hp_X]/1 g; SODIUM DIETHYL OXALACETATE 6 [hp_X]/1 g; SUS SCROFA PLACENTA 2 [hp_X]/1 g; TOXICODENDRON PUBESCENS LEAF 2 [hp_X]/1 g; SANGUINARIA CANADENSIS ROOT 2 [hp_X]/1 g; SILICON DIOXIDE 6 [hp_X]/1 g; SULFUR 6 [hp_X]/1 g; CORIANDER 8 [hp_X]/1 g
INACTIVE INGREDIENTS: CETOSTEARYL ALCOHOL; ALCOHOL; PARAFFIN; WHITE PETROLATUM

Zeel

Warnings:

For external use only. Do not use if
pregnant or breast-feeding. Do not apply over open
wounds or broken skin. In rare cases, allergic skin reactions
may develop. Keep out of reach of children. If
symptoms persist or worsen a healthcare provider should be
consulted. If swallowed, get medical help or contact a
Poison Control Center right away. Do not use if known
sensitivity to Zeel® or any of its ingredients exists.

Directions:

Adults: Apply generously to affected areas
2 to 3 times daily, or as directed by your health professional.
Massage thoroughly into skin. Children under 18 years
of age: consult your healthcare professional.
Indications: For the temporary relief of minor arthritis
pain and joint stiffness

Inactive ingredients:

Cetostearyl alcohol, Paraffin, Ethanol, Puriffied water, White Petrolatum

KEEP OUT OF REACH OF CHILDREN

Indications:

For the temporary relief of minor arthritis pain and joint stuffness.

Purpose

Arthritis Pain Relief

Active Ingrendent

Each 100 g contains: _-Lipoicum acidum
6X 0.01g, *Arnica montana, radix 2X 0.3g, *Cartilago suis 2X
0.001g (Final concentration 7X), Coenzyme A 6X 0.01g, *Dulcamara
2X 0.08g, *Embryo suis 2X 0.001g (Final concentration 7X),
*Funiculus umbilicalis suis 2X 0.001g (Final concentration 7X)
Nadidum 6X 0.01g, Natrum oxalaceticum 6X 0.01g, *Placenta
totalis suis 2X 0.001g (Final concentration 7X), *Rhus toxicodendron
2X 0.27g (Final concentration 4X), *Sanguinaria canadensis 2X
0.23g (Final concentration 4X), *Silicea 6X 1g, *Sulphur 6X 0.27g,
*Symphytum officinale 8X 0.75g. *Natural Ingredient